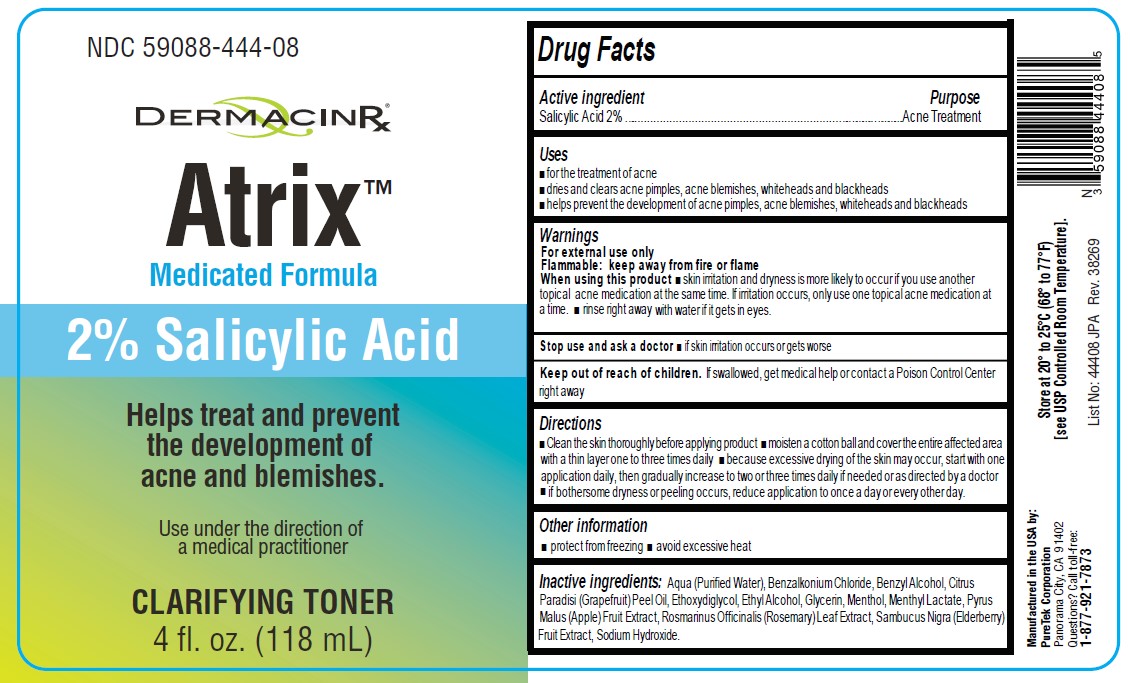 DRUG LABEL: Atrix Clarifying Toner
NDC: 59088-444 | Form: LIQUID
Manufacturer: PureTek Corporation
Category: otc | Type: HUMAN OTC DRUG LABEL
Date: 20241002

ACTIVE INGREDIENTS: SALICYLIC ACID 20 mg/1 mL
INACTIVE INGREDIENTS: WATER; BENZALKONIUM CHLORIDE; BENZYL ALCOHOL; GRAPEFRUIT OIL; DIETHYLENE GLYCOL MONOETHYL ETHER; ALCOHOL; GLYCERIN; MENTHOL, UNSPECIFIED FORM; MENTHYL LACTATE, (-)-; APPLE; ROSEMARY; EUROPEAN ELDERBERRY; SODIUM HYDROXIDE

Atrix™ Clarifying Toner

Drug Facts

Active ingredient

Salicylic Acid (2%)

Purpose

Acne Treatment

Use

■ for the treatment of acne
■ dries and clears acne pimples, acne blemishes, whiteheads and blackheads
■ helps prevent the development of acne pimples, acne blemishes, whiteheads and blackheads

Warnings

For external use only.

Flammable: Keep away from fire or flame.

When using this product

■ skin irritation and dryness is more likely to occur if you use another
topical acne medication at the same time. If irritation occurs, only use one topical acne medication at
a time. ■ rinse right away with water if it gets in eyes.

Stop use and ask a doctor

■ if skin irritation occurs or gets worse

Keep out of reach of children.

If swallowed, get medical help or contact a Poison Control Center right away.

Directions

■ Clean the skin thoroughly before applying product ■ moisten a cotton ball and cover the entire affected area with a thin layer one to three times daily ■ because excessive drying of the skin may occur, start with one application daily, then gradually increase to two or three times daily if needed or as directed by a doctor ■ if bothersome dryness or peeling occurs, reduce application to once a day or every other day.

Use under the direction of a medical practitioner.

Other information

■ protect from freezing ■ avoid excessive heat

Store at 20° to 25°C (68° to 77°F)
[see USP Controlled Room Temperature].

Questions? Call toll-free:
1-877-921-7873

Inactive ingredients

Aqua (Purified Water), Benzalkonium Chloride, Benzyl Alcohol, Citrus Paradisi (Grapefruit) Peel Oil, Ethoxydiglycol, Ethyl Alcohol, Glycerin, Menthol, Menthyl Lactate, Pyrus Malus (Apple) Fruit Extract, Rosmarinus Officinalis (Rosemary) Leaf Extract, Sambucus Nigra (Elderberry) Fruit Extract, Sodium Hydroxide.

Atrix™ Clarifying Toner

Manufactured in the USA by:
PureTek Corporation
Panorama City, CA 91402